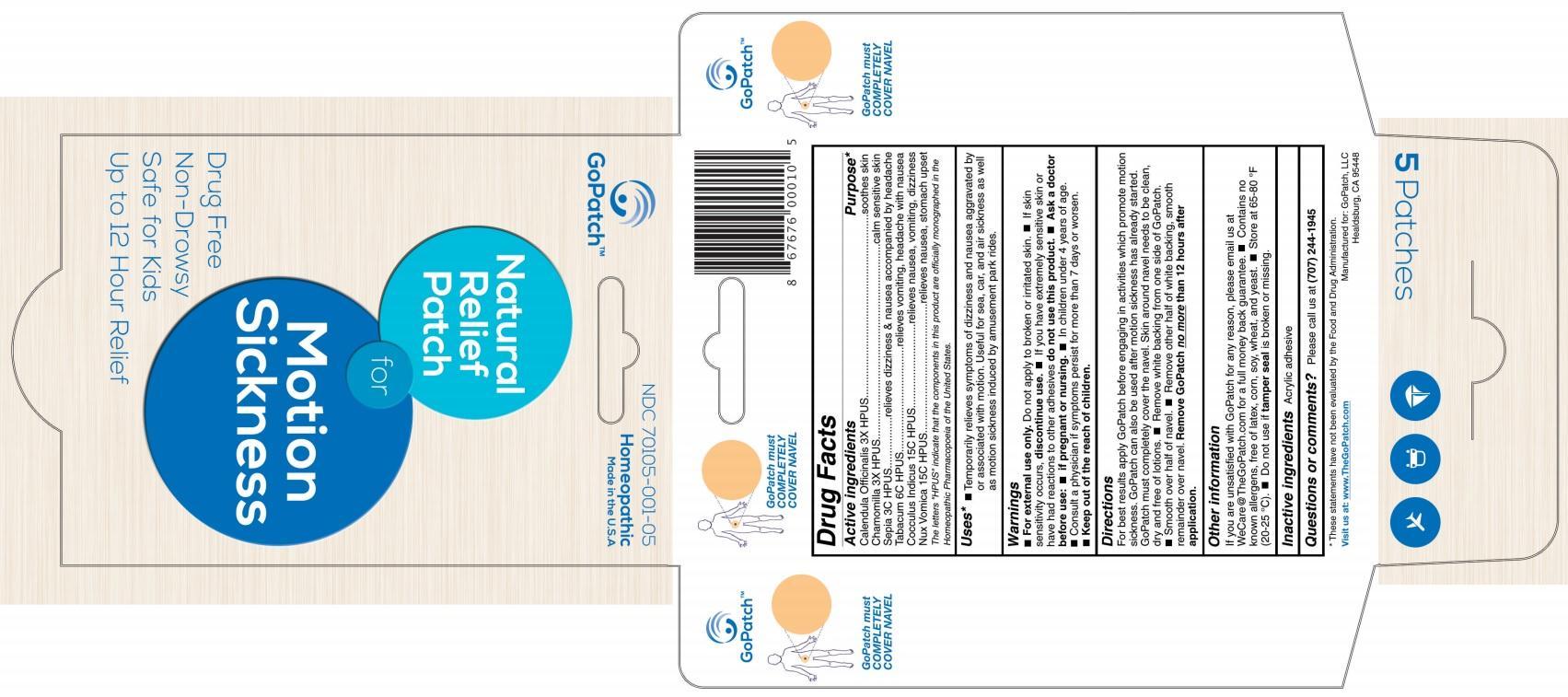 DRUG LABEL: Natural Relief Patch for MOTION SICKNESS
NDC: 70105-001 | Form: PATCH
Manufacturer: Centered Enterprises, LLC
Category: homeopathic | Type: HUMAN OTC DRUG LABEL
Date: 20240115

ACTIVE INGREDIENTS: CALENDULA OFFICINALIS FLOWERING TOP 3 [hp_X]/1 1; MATRICARIA RECUTITA 3 [hp_X]/1 1; SEPIA OFFICINALIS JUICE 3 [hp_C]/1 1; TOBACCO LEAF 6 [hp_C]/1 1; ANAMIRTA COCCULUS SEED 15 [hp_C]/1 1; STRYCHNOS NUX-VOMICA SEED 15 [hp_C]/1 1
INACTIVE INGREDIENTS: WATER; ALCOHOL; POLYVINYL ACETATE

MOTION SICKNESS

Active ingredients | Purpose*
Calendula Officinalis 3X HPUS | soothes skin
Chamomilla 3X HPUS | calm sensitive skin
Sepia 3C HPUS | relieves dizziness & nausea accompanies by headache
Tabacum 6C HPUS | relieves vomiting, headache with nausea
Cocculus Indicus 15C HPUS | relieves nausea, vomiting, dizziness
Nux Vomica 15C HPUS | relieves nausea, stomach upset

The letters "HPUS" indicate that the components in this product are officially monographed in the Homeopathic Pharmacopoeia of the United States.

Uses*

- Temporarily relieves symptoms of dizziness and nausea aggrevated by or associated with motion. Useful for sea, car, and air sickness as well as motion sickness induced by amusement park rides.

Warnings

- For external use only. Do not apply to broken or irritated skin.
- If skin sensitivity occurs, discontinue use.
- If you have extremely sensitive skin or have had reactions to other adhesives do not use this product.
- Ask a doctor before use: if pregnant or nursing; In children under 4 years of age.
- Consult a physician if symptoms persist for more than 7 days or worsen.

- Keep out of the reach of children.

Directions

For best results apply GoPatch before engaging in activities which promote motion sickness. GoPatch can also be used after motion sickness has already started. GoPatch must completely cover the navel. Skin around nevel needs to be clean, dry and free of lotions.

- Remove white backing from one side of GoPatch.
- Smooth over half of navel.
- Remove other half of white backing, smooth remainder over navel.

Remove GoPatch no more than 12 hours after application .

Other information

If you are unsatisfied with GoPatch for any reason, please email us at WeCare@TheGoPatch.com for full money back guarantee.

- Contains no known allergens, free of latex, corn, soy, wheat, and yeast.
- Store at 65-80°F (20-25°C).
- Do not use if tamper seal is broken or missing.

Inactive ingredients Acrylic adhesive

Questions or comments? Please call us at (707) 244-1945

OTHER SAFETY INFORMATION

* These statements have not been evaluated by the Food and Drug Administration.

Visit us at: www.TheGoPatch.com

Manufactured for: GoPatch, LLC

Healdsburg, CA 95448

GoPatch must COMPLETELY COVER NAVEL

PACKAGE LABEL

GoPatch™

NDC 70105-001-05

Homeopathic

Made in the U.S.A.

Natural Relief Patch for Motion Sickness

Drug Free

Non-Drowsy

Safe for Kids

Up to 12 Hour Relief

5 Patches

PURPOSE

Temporarily relieves symptoms of dizziness and nausea aggrevated by or associated with motion. Useful for sea, car, and air sickness as well as motion sickness induced by amusement park rides.